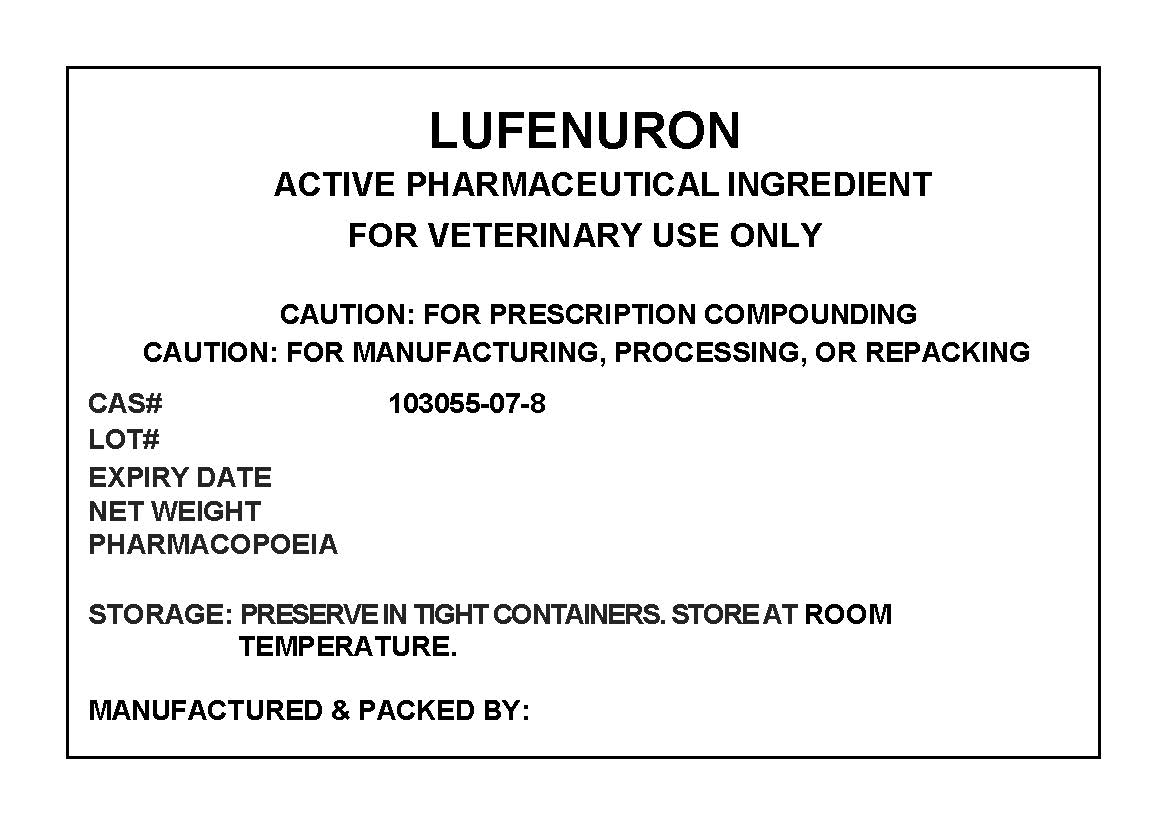 DRUG LABEL: LUFENURON
NDC: 72969-114 | Form: POWDER
Manufacturer: PROFESSIONAL GROUP OF PHARMACISTS NEW YORK LLC
Category: other | Type: BULK INGREDIENT
Date: 20210813

ACTIVE INGREDIENTS: LUFENURON 1 g/1 g

LUFENURON

PACKAGE LABEL

lufenuronlabel.jpg